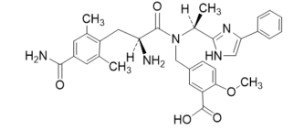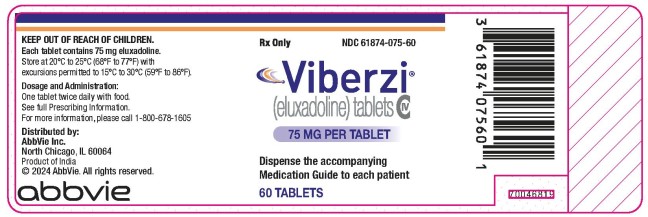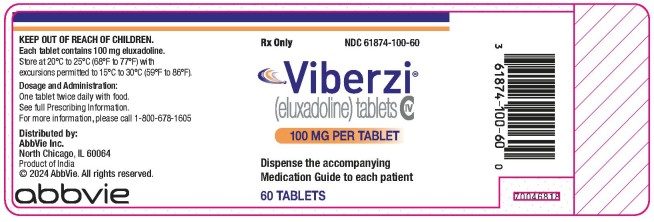 DRUG LABEL: Viberzi
NDC: 61874-075 | Form: TABLET, FILM COATED
Manufacturer: Allergan, Inc.
Category: prescription | Type: HUMAN PRESCRIPTION DRUG LABEL
Date: 20240716
DEA Schedule: CIV

ACTIVE INGREDIENTS: ELUXADOLINE 75 mg/1 1
INACTIVE INGREDIENTS: MICROCRYSTALLINE CELLULOSE; SILICON DIOXIDE; CROSPOVIDONE, UNSPECIFIED; MANNITOL; MAGNESIUM STEARATE; POLYVINYL ALCOHOL, UNSPECIFIED; TITANIUM DIOXIDE; POLYETHYLENE GLYCOL, UNSPECIFIED; TALC; FERRIC OXIDE YELLOW; FERRIC OXIDE RED

HIGHLIGHTS OF PRESCRIBING INFORMATION

These highlights do not include all the information needed to use VIBERZI safely and effectively. See full prescribing information for VIBERZI.
VIBERZI (eluxadoline) tablets, for oral use, CIV
Initial U.S. Approval: 2015

1 INDICATIONS AND USAGE

VIBERZI is a mu-opioid receptor agonist, indicated in adults for the treatment of irritable bowel syndrome with diarrhea (IBS-D). (1)

2 DOSAGE AND ADMINISTRATION

- The recommended dosage in adults is 100 mg twice daily taken with food. (2)
- The recommended dosage is 75 mg twice daily taken with food in patients:
  - unable to tolerate the 100 mg dose. (2, 6.1)
  - receiving concomitant OATP1B1 inhibitors. (2, 7)
  - with mild or moderate hepatic impairment. (2, 8.6)
  - with moderate or severe renal impairment; and in patients with end stage renal disease not yet on dialysis. (2, 8.7)
- Discontinue VIBERZI in patients who develop severe constipation. (2)
- If a dose is missed, take the next dose at the regular time; do not take 2 doses at once. (2)

3 DOSAGE FORMS AND STRENGTHS

Tablets: 75 mg and 100 mg (3)

4 CONTRAINDICATIONS

- patients without a gallbladder (4)
- known or suspected biliary duct obstruction, or sphincter of Oddi disease or dysfunction (4)
- alcoholism, alcohol abuse, alcohol addiction, or drink more than 3 alcoholic beverages/day (4)
- a history of pancreatitis; structural diseases of the pancreas, including known or suspected pancreatic duct obstruction (4)
- patients with a known hypersensitivity reaction to VIBERZI (4, 5.3)
- severe hepatic impairment (Child-Pugh Class C) (4, 8.6)
- a history of chronic or severe constipation or sequelae from constipation, or known or suspected mechanical gastrointestinal obstruction (4)

5 WARNINGS AND PRECAUTIONS

- Pancreatitis and Sphincter of Oddi Spasm: Monitor patients for new or worsening abdominal pain, with or without nausea and vomiting, or acute biliary pain with liver or pancreatic enzyme elevations; immediately discontinue VIBERZI and seek medical attention if symptoms develop. (5.1, 5.2)
- Hypersensitivity Reactions, including anaphylaxis: Immediately discontinue VIBERZI and seek medical attention if symptoms develop. (4, 5.3)
- Constipation: Instruct patients to stop VIBERZI and immediately contact their healthcare provider if they develop severe constipation. Avoid use with other drugs that may cause constipation (5.4, 7)

6 ADVERSE REACTIONS

Most common adverse reactions (>5%) are constipation, nausea and abdominal pain. (6.1)

To report SUSPECTED ADVERSE REACTIONS, contact AbbVie at 1- 800-678-1605 or FDA at 1-800-FDA-1088 or www.fda.gov/medwatch.

7 DRUG INTERACTIONS

See full prescribing information for clinically relevant interactions. (7)

FULL PRESCRIBING INFORMATION

1 INDICATIONS AND USAGE

VIBERZI is indicated in adults for the treatment of irritable bowel syndrome with diarrhea (IBS-D).

2 DOSAGE AND ADMINISTRATION

The recommended dosage of VIBERZI is 100 mg taken orally twice daily with food.

The recommended dosage of VIBERZI is 75 mg taken orally twice daily with food in patients:

- unable to tolerate the 100 mg dose of VIBERZI [see Adverse Reactions (6.1)].
- receiving concomitant OATP1B1 inhibitors [see Drug Interactions (7)].
- with mild (Child-Pugh Class A) or moderate (Child-Pugh Class B) hepatic impairment [see Use in Specific Populations (8.6)].
- with moderate or severe renal impairment (eGFR less than 60 mL/min/1.73 m^2); and in patients with end stage renal disease (ESRD) not yet on dialysis (eGFR less than 15 mL/min/1.73 m^2) [see Use in Specific Populations (8.7)].

Discontinue VIBERZI in patients who develop severe constipation [see Warnings and Precautions (5.4)].

Instruct patients if they miss a dose, take the next dose at the regular time and not to take 2 doses at the same time to make up for a missed dose.

3 DOSAGE FORMS AND STRENGTHS

- 75 mg tablets: capsule-shaped tablets are coated in pale-yellow to light tan color debossed with “FX75” on one side. Each tablet contains 75 mg eluxadoline.
- 100 mg tablets: capsule-shaped tablets are coated in pink-orange to peach color debossed with “FX100” on one side. Each tablet contains 100 mg eluxadoline.

4 CONTRAINDICATIONS

VIBERZI is contraindicated in patients:

- Without a gallbladder. These patients are at increased risk of developing serious adverse reactions of pancreatitis and/or sphincter of Oddi spasm [see Warnings and Precautions (5.1, 5.2)]
- With known or suspected biliary duct obstruction; or sphincter of Oddi disease or dysfunction. These patients are at increased risk for sphincter of Oddi spasm [see Warnings and Precautions (5.1)].
- With alcoholism, alcohol abuse or alcohol addiction, or in patients who drink more than 3 alcoholic beverages per day. These patients are at increased risk for acute pancreatitis [see Warnings and Precautions (5.1)].
- With a history of pancreatitis; or structural diseases of the pancreas, including known or suspected pancreatic duct obstruction. These patients are at increased risk for acute pancreatitis [see Warnings and Precautions (5.1)].
- With a known hypersensitivity reaction to VIBERZI [see Warnings and Precautions (5.3)].
- With severe hepatic impairment (Child-Pugh Class C). These patients are at risk for significantly increased plasma concentrations of eluxadoline [see Use in Specific Populations (8.6)]
- With a history of chronic or severe constipation or sequelae from constipation, or known or suspected mechanical gastrointestinal obstruction. These patients may be at risk for severe complications of bowel obstruction [see Warnings and Precautions (5.4)].

5 WARNINGS AND PRECAUTIONS

5.1 Pancreatitis

Pancreatitis, with or without sphincter of Oddi spasm [see Warnings and Precautions (5.1)], has been reported in patients taking either the 75 mg or 100 mg dosage of VIBERZI, including serious cases resulting in hospitalization, primarily in patients without a gallbladder. Fatal cases have also been reported in patients without a gallbladder. VIBERZI is contraindicated in patients without a gallbladder [see Contraindications (4)]. Most of the reported cases of serious pancreatitis occurred within a week of starting treatment with VIBERZI and some developed symptoms after one to two doses.

In patients with a gallbladder, evaluate a patient’s alcohol intake prior to starting VIBERZI. Instruct patients to avoid chronic or acute excessive alcohol use while taking VIBERZI. Monitor for new or worsening abdominal pain that may radiate to the back or shoulder, with or without nausea and vomiting. Instruct patients to immediately stop VIBERZI and seek medical attention if they experience symptoms suggestive of pancreatitis such as acute abdominal or epigastric pain radiating to the back or shoulder associated with elevations of pancreatic enzymes with or without nausea and vomiting [see Contraindications (4)].

5.2 Sphincter of Oddi Spasm

There is a risk of sphincter of Oddi spasm, resulting in pancreatitis or hepatic enzyme elevation associated with acute abdominal pain (e.g., biliary-type pain) in patients taking VIBERZI [see Adverse Reactions (6.1)]. Postmarketing serious adverse reactions of sphincter of Oddi spasm with or without pancreatitis resulting in hospitalization have been reported, primarily in patients without a gallbladder [see Warnings and Precautions (5.1)]. Most of the reported cases of serious sphincter of Oddi spasm occurred within a week of starting treatment with VIBERZI and some developed symptoms after one to two doses. VIBERZI is contraindicated in patients without a gallbladder [see Contraindications (4)].

Instruct patients to immediately stop VIBERZI and seek medical attention if they experience symptoms suggestive of sphincter of Oddi spasm such as acute worsening of abdominal pain, (e.g. acute epigastric or biliary [i.e., right upper quadrant] pain), that may radiate to the back or shoulder with or without nausea and vomiting, associated with elevations of pancreatic enzymes or liver transaminases. Do not restart VIBERZI in patients who developed biliary duct obstruction or sphincter of Oddi spasm while taking VIBERZI [see Contraindications (4)].

5.3 Hypersensitivity Reactions

In postmarketing experience, serious hypersensitivity reactions (including anaphylaxis) have been reported following VIBERZI administration. Some of these reactions occurred after the first one or two doses of VIBERZI [see Adverse Reactions (6.2)].

Instruct patients to immediately stop VIBERZI and seek medical attention if they experience symptoms suggestive of a hypersensitivity reaction [see Contraindications (4)].

5.4 Constipation

Constipation, sometimes requiring hospitalization, has been reported following VIBERZI administration. In postmarketing experience, severe cases with development of intestinal obstruction, intestinal perforation, and fecal impaction, requiring intervention, have also been reported. Instruct patients to stop VIBERZI and immediately contact their healthcare provider if they experience severe constipation. Avoid use with other drugs that may cause constipation [see Adverse Reactions (6.1), Drug Interactions (7)].

6 ADVERSE REACTIONS

The following adverse reactions described below and elsewhere in the labeling include:

- Pancreatitis [see Warnings and Precautions (5.1)]
- Sphincter of Oddi Spasm [see Warnings and Precautions (5.2)]
- Hypersensitivity Reactions [see Warnings and Precautions (5.3)]
- Constipation [see Warnings and Precautions (5.4)]

6.1 Clinical Trials Experience

Because clinical trials are conducted under widely varying conditions, adverse reaction rates in the clinical trials of a drug cannot be directly compared to rates in the clinical trials of another drug and may not reflect the rates observed in practice.

Over 1700 patients with IBS-D have been treated with 75 or 100 mg of VIBERZI twice daily in controlled trials. Exposures from placebo-controlled clinical trials in adult patients with IBS-D included 1391 exposed for 3 months, 1001 exposed for 6 months and 488 exposed for one year.

Demographic characteristics were comparable between the treatment groups [see Clinical Studies (14)]. Data described below represent pooled data compared to placebo across the randomized trials.

Pancreatitis

Cases of pancreatitis, not associated with sphincter of Oddi spasm, were reported in 2/807 (0.2%) of patients receiving 75 mg and 3/1032 (0.3%) of patients receiving 100 mg VIBERZI twice daily in clinical trials. Of these 5 cases, 3 were associated with excessive alcohol intake, one was associated with biliary sludge, and in one case the patient discontinued VIBERZI 2 weeks prior to the onset of symptoms. All pancreatic events resolved with lipase normalization upon discontinuation of VIBERZI, with 80% (4/5) resolving within 1 week of treatment discontinuation. The case of sphincter of Oddi spasm-induced pancreatitis resolved within 24 hours of discontinuation.

Sphincter of Oddi Spasm

In clinical trials, sphincter of Oddi spasm occurred in 0.2% (2/807) of patients receiving 75 mg and 0.8% (8/1032) of patients receiving 100 mg VIBERZI twice daily.

- Among patients receiving 75 mg, 1/807 (0.1%) patient experienced a sphincter of Oddi spasm presenting with abdominal pain but with lipase elevation less than 3 times the upper limit of normal (ULN) and 1/ 807 (0.1%) patient experienced a sphincter of Oddi spasm manifested as elevated hepatic enzymes associated with abdominal pain
- Among patients receiving 100 mg, 1/1032 (0.1%) patient experienced a sphincter of Oddi spasm manifested as pancreatitis and 7/1032 (0.7%) patients experienced sphincter of Oddi spasm manifested as elevated hepatic enzymes associated with abdominal pain

Of those patients who experienced a sphincter of Oddi spasm, 80% (8/10) reported their first onset of symptoms within the first week of treatment. The case of sphincter of Oddi spasm-induced pancreatitis occurred within minutes of taking the first dose of VIBERZI. No cases of sphincter of Oddi spasm occurred greater than 1 month after treatment onset. All events resolved upon discontinuation of VIBERZI, with symptoms typically improved by the following day.

Common Adverse Reactions

Table 1 provides the incidence of common adverse reactions reported in > 2% of IBS-D patients in either VIBERZI treatment group and at an incidence greater than in the placebo group.

Table 1: Common* Adverse Reactions in the Placebo-Controlled Studies in IBS-D Patients
Adverse Reactions | VIBERZI 100 mg twice daily (N= 1032) % | VIBERZI 75 mg twice daily (N=807) % | Placebo (N=975) %
Constipation | 8 | 7 | 2
Nausea | 7 | 8 | 5
Abdominal Pain** | 7 | 6 | 4
Upper Respiratory Tract Infection | 5 | 3 | 4
Vomiting | 4 | 4 | 1
Nasopharyngitis | 3 | 4 | 3
Abdominal Distention | 3 | 3 | 2
Bronchitis | 3 | 3 | 2
Dizziness | 3 | 3 | 2
Flatulence | 3 | 3 | 2
Rash*** | 3 | 3 | 2
Increased ALT | 3 | 2 | 1
Fatigue | 2 | 3 | 2
Viral gastroenteritis | 1 | 3 | 2

* Reported in > 2% of VIBERZI-treated patients at either dose and at an incidence greater than in placebo-treated patients

**"Abdominal Pain" term includes: abdominal pain, abdominal pain lower, and abdominal pain upper

*** "Rash" term includes: dermatitis, dermatitis allergic, rash, rash erythematous, rash generalized, rash maculo-papular, rash papular, rash pruritic, urticaria, and idiopathic urticaria

Constipation was the most commonly reported adverse reaction in VIBERZI-treated patients in these trials. Approximately 50% of constipation events occurred within the first 2 weeks of treatment while the majority occurred within the first 3 months of therapy. Rates of severe constipation were less than 1% in patients receiving 75 mg and 100 mg VIBERZI. Similar rates of constipation occurred between the active and placebo arms beyond 3 months of treatment.

Adverse Reactions Leading to Discontinuation

Eight percent of patients treated with 75 mg, 8% of patients treated with 100 mg VIBERZI and 4% of patients treated with placebo discontinued prematurely due to adverse reactions. In the VIBERZI treatment groups, the most common reasons for discontinuation due to adverse reactions were constipation (1% for 75 mg and 2% for 100 mg) and abdominal pain (1% for both 75 mg and 100 mg). In comparison, less than 1% of patients in the placebo group withdrew due to constipation or abdominal pain.

Less Common Adverse Reactions

Adverse reactions that were reported in ≤ 2% of VIBERZI-treated patients are listed below by body system.

Gastrointestinal: gastroesophageal reflux disease
General Disorders and administration site conditions: feeling drunk
Investigations: increased AST
Nervous system: sedation, somnolence
Psychiatric disorders: euphoric mood
Respiratory: asthma, bronchospasm, respiratory failure, wheezing

6.2 Postmarketing Experience

The following adverse reactions have been identified during post-approval use of VIBERZI. Because these reactions are reported voluntarily from a population of uncertain size, it is not always possible to reliably estimate their frequency or establish a causal relationship to drug exposure.

Hypersensitivity: anaphylaxis, angioedema (e.g. swollen face and throat), dyspnea, throat tightness, and chest pain/tightness [see Warnings and Precautions (5.3)].

7 DRUG INTERACTIONS

Tables 2 and 3 include drugs which demonstrated a clinically important drug interaction with VIBERZI or which potentially may result in clinically relevant interactions.

Table 2: Established and Other Potentially Clinically Relevant Interactions Affecting VIBERZI
OATP1B1 Inhibitors
Clinical Impact: | Increased exposure to eluxadoline when coadministered with cyclosporine [see Clinical Pharmacology (12.3)]
Intervention: | Administer VIBERZI at a dose of 75 mg twice daily [see Dosage and Administration (2)] and monitor patients for impaired mental or physical abilities needed to perform potentially hazardous activities such as driving a car or operating machinery and for other eluxadoline-related adverse reactions [see Adverse Reactions (6.1)].
Examples: | cyclosporine, gemfibrozil, antiretrovirals (atazanavir, lopinavir, ritonavir, saquinavir, tipranavir), rifampin, eltrombopag
Drugs that Cause Constipation
Clinical Impact: | Increased risk for constipation related adverse reactions and potential for constipation related serious adverse reactions
Intervention: | Avoid use with other drugs that may cause constipation (see below); loperamide may be used occasionally for acute management of severe diarrhea but avoid chronic use. Discontinue loperamide immediately if constipation occurs.
Examples: | alosetron, anticholinergics, opioids

Table 3: Established and Other Potentially Clinically Relevant Interactions Affecting Drugs Co-Administered with VIBERZI
OATP1B1 and BCRP Substrate
Clinical Impact: | VIBERZI may increase the exposure of co-administered OATP1B1 and BCRP substrates. Increased exposure to rosuvastatin when co-administered with VIBERZI with a potential for increased risk of myopathy/rhabdomyolysis [see Clinical Pharmacology (12.3)]
Intervention: | Use the lowest effective dose of rosuvastatin (see prescribing information of rosuvastatin for additional information on recommended dosing).

8 USE IN SPECIFIC POPULATIONS

8.1 Pregnancy

Risk Summary

There are no studies with VIBERZI in pregnant women that inform any drug-associated risks. The background risk of major birth defects and miscarriage for the indicated population is unknown. However, the background risk in the U.S. general population of major birth defects is 2 to 4% and of miscarriage is 15 to 20% of clinically recognized pregnancies. In animal reproduction studies, oral and subcutaneous administration of eluxadoline to rats and rabbits during organogenesis at doses approximately 51 and 115 times the human exposure after a single oral dose of 100 mg, respectively, demonstrated no teratogenic effects. In a pre- and postnatal development study in rats, no adverse effects were observed in offspring with oral administration of eluxadoline at doses approximately 10 times the human exposure (see Data).

Data

Animal Data

Eluxadoline administered as combined oral (1000 mg/kg/day) and subcutaneous (5 mg/kg/day) doses during the period of organogenesis to rats and rabbits (exposures about 51 and 115 times, respectively, the human AUC of 24 ng.h/mL after a single oral dose of 100 mg) did not cause any adverse effects on embryofetal development. A pre- and postnatal development study in rats showed no evidence of any adverse effect on pre- and postnatal development at oral doses of eluxadoline up to 1000 mg/kg/day (with exposures about 10 times the human AUC of 24 ng.h/mL after a single oral dose of 100 mg). In the same study, eluxadoline was detected in the milk of lactating rats administered oral doses of 100, 300 and 1000 mg/kg/day (with exposures about 1.8, 3 and 10 times, respectively, the human AUC of 24 ng.h/mL after a single oral dose of 100 mg). Milk samples were collected from six lactating females per group on lactation day 12. Mean concentrations of eluxadoline in the milk of lactating rats on lactation day 12 were 2.78, 5.49 and 44.02 ng/mL at 100, 300 and 1000 mg/kg/day, respectively.

8.2 Lactation

Risk Summary

No data are available regarding the presence of eluxadoline in human milk, the effects of eluxadoline on the breastfed infant, or the effects of eluxadoline on milk production. However, eluxadoline is present in rat milk [see Use in Specific Populations (8.1)].

The developmental and health benefits of breastfeeding should be considered along with the mother’s clinical need for VIBERZI and any potential adverse effects on the breastfed infant from VIBERZI or from the underlying maternal condition.

8.4 Pediatric Use

Safety and effectiveness in pediatric patients have not been established.

Juvenile Toxicology Data

Eluxadoline was orally administered to juvenile rats at 500, 750, and 1500 mg/kg/day (about 16, 54 and 30 times, respectively, the human AUC of 24 ng.h/mL after a single oral dose of 100 mg) for 4 weeks. There were no adverse physiologic effects related to eluxadoline. Based on these results, the NOAEL for male and female juvenile rats was 1500 mg/kg/day (about 30 times the human AUC of 24 ng.h/mL after a single oral dose of 100 mg).

8.5 Geriatric Use

Of 1795 IBS-D patients in clinical trials of VIBERZI who received 75 mg or 100 mg twice daily, 139 (7.7%) were at least 65 years of age, while 15 (0.8%) were at least 75 years old. No overall differences in effectiveness were observed between these patients and younger patients. There were no overall differences in the types of adverse reactions observed between elderly and younger patients; however, a higher proportion of elderly patients than younger patients experienced adverse reactions (66% vs 59%), serious adverse reactions (9% vs 4%), and gastrointestinal adverse reactions (39% vs 28%).

8.6 Hepatic Impairment

Plasma concentrations of eluxadoline increase in patients with hepatic impairment [see Clinical Pharmacology (12.3)].

VIBERZI is contraindicated in patients with severe hepatic impairment (Child-Pugh Class C) as plasma concentrations of eluxadoline increase significantly (16-fold) and there is no information to support the safety of VIBERZI in these patients.

In patients with mild (Child-Pugh Class A) or moderate (Child-Pugh Class B) hepatic impairment, plasma concentrations of eluxadoline increase to a lesser extent (6- and 4-fold, respectively). Administer VIBERZI at a reduced dose of 75 mg twice daily to these patients [see Dosage and Administration (2)]. Monitor patients with any degree of hepatic impairment for impaired mental or physical abilities needed to perform potentially hazardous activities such as driving a car or operating machinery and for other eluxadoline-related adverse reactions [see Adverse Reactions (6.1)].

8.7 Renal Impairment

In patients with severe renal impairment (eGFR 15 to 30 mL/min/1.73 m^2) and ESRD not yet on dialysis (eGFR less than 15 mL/min/1.73 m^2), exposure of eluxadoline was increased compared to healthy subjects with normal renal function [see Clinical Pharmacology (12.3)]. Administer VIBERZI at a reduced dose of 75 mg twice daily to patients with moderate or severe renal impairment and in patients with ESRD not yet on dialysis [see Dosage and Administration (2)]. No dosage adjustment is needed for patients with mild renal impairment.

9 DRUG ABUSE AND DEPENDENCE

9.1 Controlled Substance

Eluxadoline is listed in Schedule IV of the Controlled Substances Act.

9.2 Abuse

In a drug discrimination study in monkeys, intravenous administration of eluxadoline hydrochloride produced full generalization to the morphine cue. In a self-administration study in monkeys, eluxadoline hydrochloride was self-administered to a degree that was less than that of heroin but greater than that of saline.

Adverse reactions of euphoria and feeling drunk were reported in clinical trials of IBS-D evaluating 75 mg and 100 mg doses of VIBERZI. The rate of euphoria was 0% for 75 mg and 0.2% (2/1032) for 100 mg and the rate of feeling drunk was 0.1% (1/807) for 75 mg and 0.1% (1/1032) for 100 mg.

In contrast, in two human abuse potential studies conducted in recreational opioid-experienced individuals, supratherapeutic oral doses of VIBERZI (300 mg and/or 1000 mg) and intranasal doses of VIBERZI (100 mg and/or 200 mg) produced the adverse reaction of euphoria (at a rate ranging from 14% to 28%) that was greater than that of placebo (0% to 5%) but less than that of oxycodone (44% to 76%). In the two human abuse potential studies, supratherapeutic oral and intranasal doses of VIBERZI produced small but significant increases on positive subjective measures such as Drug Liking and High compared to placebo. Supratherapeutic oral and intranasal doses of VIBERZI also produced small but significant increases on negative subjective measures such as Drug Disliking and Dysphoria compared to placebo. In the same studies, oxycodone (30 mg and 60 mg oral, and 15 and 30 mg intranasal) produced significantly greater responses on positive and negative subjective measures than those produced by eluxadoline and placebo.

9.3 Dependence

In studies with monkeys and rats in which eluxadoline and eluxadoline hydrochloride were chronically administered, discontinuation of the drug did not lead to behavioral signs of withdrawal, a measure of physical dependence. However, the ability of eluxadoline hydrochloride in monkeys to induce self-administration suggests that the drug is sufficiently rewarding to produce reinforcement. In two human abuse potential studies with VIBERZI conducted in recreational opioid-experienced individuals, euphoria was reported at a rate of 14% to 28%. These data suggest that eluxadoline may produce psychological dependence.

10 OVERDOSAGE

No reports of overdosage with VIBERZI have been reported.

In the event of acute overdose, the stomach should be emptied and adequate hydration maintained. The patient should be carefully observed and given standard supportive treatment as required. Given eluxadoline’s action at opioid receptors, administration of a narcotic mu-opioid antagonist, such as naloxone, should be considered. Considering the short half-life of naloxone, repeated administration may be necessary. In the event of naloxone administration, subjects should be monitored closely for the return of overdose symptoms, which may indicate need for repeated naloxone injection.

11 DESCRIPTION

The active ingredient in VIBERZI is eluxadoline, a mu-opioid receptor agonist.

The full chemical name is 5-[[[(2S)-2-amino-3-[4-(aminocarbonyl)-2,6-dimethylphenyl]-1-oxopropyl][(1S)-1-(4-phenyl-1H-imidazol-2-yl)ethyl]amino]methyl]-2-methoxybenzoic acid.

Eluxadoline has a molecular weight of 569.65 and a molecular formula of C32H35N5O5. The chemical structure of eluxadoline is:

VIBERZI is available as 75 mg and 100 mg tablets for oral administration. In addition to the active ingredient, eluxadoline, each tablet contains the following inactive ingredients: silicified microcrystalline cellulose, colloidal silica, crospovidone, mannitol, magnesium stearate, and Opadry II (partially hydrolyzed polyvinyl alcohol, titanium dioxide, polyethylene glycol, talc, iron oxide yellow, and iron oxide red).

12 CLINICAL PHARMACOLOGY

12.1 Mechanism of Action

Eluxadoline is a mu-opioid receptor agonist; eluxadoline is also a delta opioid receptor antagonist and a kappa opioid receptor agonist. The binding affinities (Ki) of eluxadoline for the human mu and delta opioid receptors are 1.8 nM and 430 nM, respectively. The binding affinity (Ki) of eluxadoline for the human kappa opioid receptor has not been determined; however, the Ki for guinea pig cerebellum kappa opioid receptor is 55 nM. In animals, eluxadoline interacts with opioid receptors in the gut.

12.2 Pharmacodynamics

Cardiac Electrophysiology

At a dose 10 times the maximum recommended dose (100 mg), VIBERZI does not prolong the QT interval to any clinically relevant extent.

12.3 Pharmacokinetics

Following oral administration of 100 mg VIBERZI in healthy subjects, the Cmax of eluxadoline was approximately 2 to 4 ng/mL and AUC was 12 to 22 ng.h/mL. Eluxadoline has approximately linear pharmacokinetics with no accumulation upon repeated twice daily dosing. The variability of eluxadoline pharmacokinetic parameters ranges from 51% to 98%.

Absorption

Absolute bioavailability of eluxadoline has not been determined.

Effect of Food

The median Tmax value was 1.5 hours (range: 1 to 8 hours) under fed conditions and 2 hours (range: 0.5 to 6 hours) under fasting conditions [see Dosage and Administration (2)].

The administration of VIBERZI with a high fat meal that contained approximately 800 to 1000 total calories, with 50% of calories being derived from fat content decreased the Cmax of eluxadoline by 50% and AUC by 60%.

Distribution

Plasma protein binding of eluxadoline was 81%.

Elimination

The mean plasma elimination half-life of eluxadoline ranged from 3.7 hours to 6 hours.

Metabolism

Cytochrome P450 (CYP) and UGT pathways have minimal involvement in the metabolism of eluxadoline. It is unlikely that metabolism of eluxadoline by these enzymes has a clinically meaningful impact on systemic exposure.

Excretion

Following a single oral dose of 300 mg [^14C] eluxadoline in healthy male subjects, 82.2% of the total radioactivity was recovered in feces within 336 hours and less than 1% was recovered in urine within 192 hours.

Specific Populations

Patients with Hepatic Impairment

Following a single oral 100–mg dose in subjects with varying degrees of liver impairment and healthy subjects, mean eluxadoline plasma exposure was 6-fold, 4-fold, and 16-fold higher in mild, moderate, and severe hepatically impaired subjects (Child Pugh Class A, B, C), respectively, compared to the subjects with normal liver function [see Dosage and Administration (2), Contraindications (4), Use in Specific Populations (8.6)].

Patients with Renal Impairment

Following a single oral 100 mg dose, the mean eluxadoline Cmax and AUC0-t were 3.7-fold and 4.7-fold higher, respectively, in subjects with severe renal impairment (eGFR 15 to 30 mL/min/1.73 m^2, n=2) and 2.4-fold and 5.9-fold higher, respectively, in subjects with ESRD not yet on dialysis (eGFR less than 15 mL/min/1.73 m^2, n=6) compared to healthy subjects with normal renal function (n=6) [see Dosage and Administration (2), Use in Specific Populations (8.7)].

Drug Interaction Studies

In Vitro Assessment of Drug Interactions

In vitro studies indicate that eluxadoline is neither an inducer of CYP1A2, CYP2C9, CYP2C19, and CYP3A4, nor an inhibitor of CYP1A2, CYP2A6, CYP2B6, CYP2C9, CYP2C19, and CYP2D6 at clinically relevant systemic concentrations. Although CYP2E1 was slightly inhibited by eluxadoline (IC50 of approximately 20 micromolar [11 mcg/mL]), clinically meaningful interactions are unlikely. Despite mechanism-based inhibition of CYP3A4 in vitro, eluxadoline did not have a clinically meaningful drug-drug interaction with the CYP3A4 substrate midazolam.

In vitro studies suggest that eluxadoline is a substrate for OAT3, OATP1B1, BSEP and MRP2, but not for OCT1, OCT2, OAT1, OATP1B3, P-gp and BCRP. Based on the in vitro studies, clinically meaningful interaction via inhibition of OCT1, OCT2, OAT1, OAT3, OATP1B3, BSEP and MRP2 by eluxadoline is unlikely.

In Vivo Assessment of Drug Interactions

The following drug interactions were studied in healthy subjects:

Oral Contraceptives

Coadministration of multiple doses of 100 mg VIBERZI with multiple dose administration of an oral contraceptive (norethindrone 0.5 mg/ethinyl estradiol 0.035 mg) does not change the exposure of either drug.

Cyclosporine

Coadministration of a single dose of 100 mg VIBERZI with a single dose of 600 mg cyclosporine resulted in 4.4-fold and 6.2-fold increase in AUC and Cmax of eluxadoline, respectively, compared to administration of VIBERZI alone [see Drug Interactions (7)].

Probenecid

Coadministration of a single dose of 100 mg VIBERZI with a single dose of 500 mg probenecid resulted in a 35% and 31% increase in eluxadoline AUC and Cmax, respectively, compared to administration of VIBERZI alone. This change in eluxadoline exposures is not expected to be clinically meaningful.

Rosuvastatin

Coadministration of multiple doses of 100 mg VIBERZI twice daily with a single dose 20 mg rosuvastatin resulted in an increase in the AUC (40%) and Cmax (18%) of rosuvastatin compared to administration of rosuvastatin alone. Similar results were observed with the active, major metabolite, n-desmethyl rosuvastatin [see Drug Interactions (7)].

Midazolam

Coadministration of multiple doses of 100 mg VIBERZI twice daily with single dose administration of 4 mg midazolam did not affect midazolam pharmacokinetics in humans, suggesting that eluxadoline will not affect the exposure of concomitantly administered CYP3A4 substrates.

13 NONCLINICAL TOXICOLOGY

13.1 Carcinogenesis, Mutagenesis, Impairment of Fertility

Carcinogenesis

Two-year oral carcinogenicity studies have been conducted with eluxadoline in CD-1 mice at doses up to 1500 mg/kg/day (about 14 times the human AUC of 24 ng.h/mL after a single oral dose of 100 mg) and in Sprague Dawley rats at oral doses up to 1500 mg/kg/day (about 36 times the human AUC of 24 ng.h/mL after a single oral dose of 100 mg). Oral administration of eluxadoline for 104 weeks did not produce tumors in mice and rats.

Mutagenesis

Eluxadoline was negative in the Ames test, chromosome aberration test in human lymphocytes, in the mouse lymphoma cell (L5178Y/TK+/-) forward mutation test and in the in vivo rat bone marrow micronucleus test.

Impairment of Fertility

Eluxadoline at oral doses up to 1000 mg/kg/day (about 10 times the human AUC of 24 ng.h/mL after a single oral dose of 100 mg) was found to have no adverse effect on fertility and reproductive performance of male and female rats.

14 CLINICAL STUDIES

The efficacy and safety of VIBERZI in IBS-D patients was established in two randomized, multi-center, multi-national, double-blind, placebo-controlled trials (Studies 1 and 2). A total of 1281 patients in Study 1 and 1145 patients in Study 2 received treatment with VIBERZI 75 mg, VIBERZI 100 mg or placebo twice daily [overall, patients had a mean age of 45 years (range 18 to 80 years with 10% at least 65 years of age or older), 66% female, 86% white, 11% black, and 27% Hispanic].

All patients met Rome III criteria for IBS-D (loose [mushy] or watery stools ≥25% and hard or lumpy stools <25% of bowel movements) and were required to meet both of the following criteria:

- an average of worst abdominal pain scores in the past 24 hours of >3.0 on a 0 to 10 scale over the week prior to randomization.
- an average daily stool consistency score (Bristol Stool Scale or BSS) of ≥5.5 and at least 5 days with a BSS score ≥5 on a 1 to 7 scale over the week prior to randomization.

Pertinent exclusion criteria included: prior pancreatitis, alcohol abuse, cholecystitis prior 6 months, sphincter of Oddi dysfunction, inflammatory bowel disease, intestinal obstruction, gastrointestinal infection or diverticulitis within prior 3 months, lipase greater than 2 xULN, ALT or AST greater than 3 xULN.

Study 1 and Study 2 included identical 26-week double-blind, placebo-controlled treatment periods. Study 1 continued double-blinded for an additional 26 weeks for long-term safety (total of 52 weeks of treatment), followed by a 2-week follow-up. Study 2 included a 4-week single-blinded, placebo-withdrawal period upon completion of the 26-week treatment period. During the double-blind treatment phase and the single-blinded placebo withdrawal phase, patients were allowed to take loperamide rescue medication for the acute treatment of uncontrolled diarrhea, but were not allowed to take any other antidiarrheal, antispasmodic agent or rifaximin for their diarrhea. Additionally, patients were allowed to take aspirin-containing medications or nonsteroidal anti-inflammatory drugs, but no narcotic or opioid containing agents.

Efficacy of VIBERZI was assessed in both trials using an overall composite responder primary endpoint. The primary endpoint was defined by the simultaneous improvement in the daily worst abdominal pain score by ≥30% as compared to the baseline weekly average AND a reduction in the BSS to <5 on at least 50% of the days within a 12-week time interval. Improvement in daily worst abdominal pain in the absence of a concurrent bowel movement was also considered a response day. Results for endpoints were based on electronic daily diary entries by patients.

The proportion of composite responders over 12 weeks is shown in Table 4. In both trials, the proportion of patients who were composite responders to VIBERZI was statistically significantly higher than placebo for both doses. The proportion of patients who were composite responders to VIBERZI was similar for male and female patients in both trials.

Table 4: Efficacy Results in Randomized Clinical Trials
 | Study 1 |  |  |  | Study 2
 | VIBERZI 100mg twice daily n=426 | VIBERZI 75mg twice daily n=427 | PBO n=427 |  | VIBERZI 100mg twice daily n=382 | VIBERZI 75mg twice daily n=381 | PBO n=382
Composite^1 Response over 12 weeks
Responder rates | 25% | 24% |  | 17% | 30% | 29% | 16%
Treatment difference | 8%^2 | 7%^4 |  |  | 13%^3 | 13%^3
95% CI (%) | (2.6, 13.5) | (1.4, 12.2) |  |  | (7.5, 19.2) | (6.8, 18.5)
Composite Response over 26 weeks
Responder rates | 29% | 23% |  | 19% | 33% | 30% | 20%
Treatment difference | 10% | 4% |  |  | 13% | 10%
95% CI (%) | (4.7, 16.1) | (-1.0, 9.9) |  |  | (6.4, 18.8) | (4.2, 16.4)
Abdominal Pain Response Improved ≥30% over 12 weeks
Responder rates | 43% | 42% |  | 40% | 51% | 48% | 45%
Treatment difference | 4% | 3% |  |  | 6% | 3%
95% CI (%) | (-3.0, 10.2) | (-3.8, 9.4) |  |  | (-1.3, 12.8) | (-4.3, 9.8)
BSS <5 Response over 12 weeks
Responder rates | 34% | 30% |  | 22% | 36% | 37% | 21%
Treatment difference | 12% | 8% |  |  | 15% | 16%
95% CI (%) | (6.3, 18.2) | (2.1, 13.8) |  |  | (8.4, 21.0) | (9.7, 22.4)

^1Composite= Simultaneous improvement of Worst Abdominal Pain (WAP) by ≥30% and Bristol Stool Score (BSS) < 5 on the same day for ≥ 50% of days over the interval

^2 P<0.01

^3 P<0.001

^4 P<0.05

Additionally, the proportion of patients who were composite responders to VIBERZI at each 4-week interval was numerically higher than placebo for both doses as early as month 1 through month 6 demonstrating that efficacy is maintained throughout the course of treatment.

During the 4 week single-blind withdrawal period in Study 2, no evidence of worsening of diarrhea or abdominal pain compared to baseline was demonstrated at either dose.

16 HOW SUPPLIED/STORAGE AND HANDLING

VIBERZI is available as:

- 75 mg tablets: capsule-shaped tablets, coated in pale-yellow to light tan color, debossed with “FX75” on one side.
  Bottle of 60: NDC 61874-075-60
- 100 mg tablets: capsule-shaped tablets, coated in pink-orange to peach color, debossed with “FX100” on one side.
  Bottle of 60: NDC 61874-100-60

Store VIBERZI tablets at 20°C to 25°C (68°F to 77°F) with excursions permitted to 15°C to 30°C (59°F to 86°F) [see USP Controlled Room Temperature].

17 PATIENT COUNSELING INFORMATION

Advise the patient to read the FDA-approved patient labeling (Medication Guide).

Instruct patients to:

- stop VIBERZI immediately and seek medical attention if unusual or severe abdominal pain that may radiate to the back or shoulder with or without nausea and vomiting, develops [see Warnings and Precautions (5.1, 5.2)].
- avoid chronic or acute excessive alcohol use while taking VIBERZI [see Warnings and Precautions (5.1)].
- stop VIBERZI immediately and seek medical attention if symptoms of a hypersensitivity reaction develop [see Warnings and Precautions (5.3)].
- stop VIBERZI and immediately call their health care provider if they experience severe constipation [see Dosage and Administration (2), Warnings and Precautions (5.4)].
- take one tablet twice daily with food.
- if they miss a dose, take the next dose at the regular time. Do not take 2 doses at the same time to make up for a missed dose.
- call their healthcare provider if they are unable to tolerate VIBERZI
- not take alosetron with VIBERZI or not take loperamide on a chronic basis with VIBERZI due to the potential for constipation. Loperamide may occasionally be used with VIBERZI for acute management of severe diarrhea, but must be discontinued if constipation develops. Also, instruct patients to avoid taking VIBERZI with other medications that may cause constipation (for example opioids, anticholinergics, etc.) [see Drug Interactions (7)].

Distributed by:
AbbVie, Inc.
North Chicago, IL 60064

VIBERZI and its design are trademarks of Allergan Holdings Unlimited Company, an AbbVie company.

© 2024 AbbVie. All rights reserved.

MEDICATION GUIDE
VIBERZI (vye BER zee), CIV
(eluxadoline) tablets

What is the most important information I should know about VIBERZI?
VIBERZI can cause serious side effects, including:

- Inflammation of the pancreas (pancreatitis). Pancreatitis has happened most often in people who do not have a gallbladder and can lead to hospitalization. Pancreatitis has led to death in some people who do not have a gallbladder. Pancreatitis usually happens within the first week of treatment with VIBERZI but can happen after 1 to 2 doses of VIBERZI. Your risk of getting pancreatitis is increased if you drink more than 3 alcoholic drinks a day. Limit your use of alcoholic drinks while you are taking VIBERZI.
- Sphincter of Oddi spasm. The sphincter of Oddi is a muscular valve that controls the flow of digestive juices (bile and pancreatic juice) to the first part of your small intestine. A sphincter of Oddi spasm can cause an increase in your liver and pancreas enzymes and inflammation of the pancreas (pancreatitis) that can cause sudden stomach-area (abdomen) pain. Sphincter of Oddi spasm has happened most often in people who do not have a gallbladder and can lead to hospitalization. This spasm usually happens within the first week of treatment with VIBERZI but can happen after 1 or 2 doses of VIBERZI.

Stop taking VIBERZI right away and get emergency medical care if you have new or worsening stomach-area (abdomen) pain or pain in the upper right side of your stomach-area (abdomen) that may move to your back or shoulder, with or without nausea and vomiting.

- Serious allergic reactions. Serious allergic reactions have happened in some people after taking 1 or 2 doses of VIBERZI. Stop taking VIBERZI right away and get emergency medical care if you have signs or symptoms of an allergic reaction, including:

○ swelling of your face, lips, mouth or tongue

○ itching

○ shortness of breath or other breathing problems

○ rash

○ hives

- Constipation. Constipation, including severe constipation that can lead to hospitalization has happened after taking VIBERZI. Stop taking VIBERZI and call your doctor right away if you develop severe constipation while taking VIBERZI.

What is VIBERZI?
VIBERZI is a prescription medicine used to treat adults who have irritable bowel syndrome with diarrhea (IBS-D).

- VIBERZI is a controlled substance (CIV) because it contains eluxadoline and may be abused or lead to drug dependence. Keep your VIBERZI in a safe place, to protect it from theft. Never give your VIBERZI to anyone else, because it may harm them. Selling or giving away this medicine is against the law.

It is not known if VIBERZI is safe and effective in children.
People 65 years old and older have had an increased number of side effects, including serious side effects and stomach problems, while taking VIBERZI than people younger than 65 years old have had.

Do not take VIBERZI if you:

- do not have a gallbladder.
- have or may have had a blockage in your gallbladder or a sphincter of Oddi problem.
- have or had problems with alcohol abuse, alcohol addiction, or drink more than 3 alcoholic drinks a day.
- have had inflammation of your pancreas (pancreatitis) or other pancreas problems, including if you have had or may have had a blockage in your pancreas.
- have had an allergic reaction to VIBERZI.
- have severe liver problems.
- have had long-lasting (chronic) or severe constipation, or problems caused by constipation.
- have or may have had a bowel blockage (intestinal obstruction).

Talk to your doctor if you are not sure if you have any of these conditions.

Before taking VIBERZI, tell your doctor about all of your medical conditions, including if you:

- See “What is the most important information I should know about VIBERZI?”
- have liver problems.
- are pregnant or plan to become pregnant. It is not known if VIBERZI will harm your unborn baby.
- are breastfeeding or plan to breastfeed. It is not known if VIBERZI passes into your breast milk or could harm your baby.

Tell your doctor about all the medicines you take, including prescription and over-the-counter medicines, vitamins, and herbal supplements. Keep a list of your medicines to show your doctor and pharmacist when you get a new medicine. VIBERZI and other medicines may affect each other causing side effects.
If you are taking VIBERZI you should not take:

- medicines that cause constipation including:
  ○ Lotronex® (alosetron)
  ○ anticholinergic medicines
  ○ opioid pain medicines

Ask your doctor or pharmacist for a list of these medicines, if you are not sure.

- Avoid taking loperamide, a medicine used to treat diarrhea, for a long time (chronic use). You may take loperamide occasionally to treat severe diarrhea. Stop taking loperamide right away if you become constipated.

How should I take VIBERZI?

- Take VIBERZI exactly as your doctor tells you to take it.
- Take 1 tablet of VIBERZI 2 times each day with food.
- If you miss a dose, take your next dose at your regular time. Do not take 2 doses at the same time to make up for a missed dose.
- Do not change your dose or stop taking VIBERZI unless your doctor tells you to.
- If you take too much VIBERZI, call your doctor or go to the nearest hospital emergency room right away.

What should I avoid while taking VIBERZI?

- Limit your use of alcoholic drinks while you are taking VIBERZI.
- If you have liver problems, do not drive, operate machinery, or do other dangerous activities until you know how VIBERZI affects you.

What are the possible side effects of VIBERZI?
See “What is the most important information I should know about VIBERZI?”
The most common side effects of VIBERZI include: constipation, nausea, and abdominal pain. Stop taking VIBERZI right away and immediately call your doctor if you have constipation that is severe.
These are not all the possible side effects of VIBERZI. Call your doctor for medical advice about side effects. You may report side effects to FDA at 1-800-FDA-1088.

How should I store VIBERZI?
Store VIBERZI at room temperature between 68°F to 77°F (20°C to 25°C).
Keep VIBERZI and all medicines out of the reach of children.

General Information about the safe and effective use of VIBERZI.
Medicines are sometimes prescribed for purposes other than those listed in a Medication Guide. Do not use VIBERZI for a condition for which it was not prescribed. Do not give VIBERZI to other people, even if they have the same symptoms that you have. It may harm them. You can ask your doctor or pharmacist for information about VIBERZI that is written for health professionals.

What are the ingredients in VIBERZI?
Active ingredient: eluxadoline
Inactive ingredients: silicified microcrystalline cellulose, colloidal silica, crospovidone, mannitol, magnesium stearate, and Opadry II (partially hydrolyzed polyvinyl alcohol, titanium dioxide, polyethylene glycol, talc, iron oxide yellow, and iron oxide red).
Distributed by: AbbVie, Inc. North Chicago, IL 60064
© 2024 AbbVie. All rights reserved.
VIBERZI and its design are trademarks of Allergan Holdings Unlimited Company, an AbbVie company.
For more information, go to www.VIBERZI.com or call 800-678-1605.

This Medication Guide has been approved by the U.S. Food and Drug Administration. Revised: July 2024

PRINCIPAL DISPLAY PANEL

NDC 61874-075-60
Viberzi®
(eluxadoline) tablets CIV
75 MG PER TABLET
Dispense the accompanying
Medication Guide to each patient
60 TABLETS
Rx Only

PRINCIPAL DISPLAY PANEL

NDC 61874-100-60
Viberzi®
(eluxadoline) tablets CIV
100 MG PER TABLET
Dispense the accompanying
Medication Guide to each patient
60 TABLETS
Rx Only